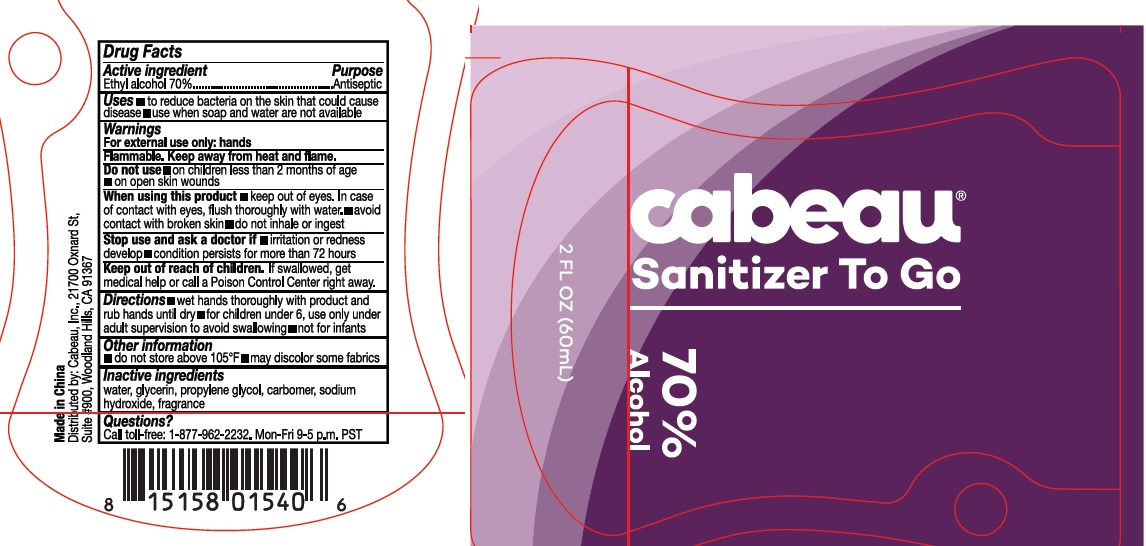 DRUG LABEL: cabeau Sanitizer To Go
NDC: 74274-014 | Form: GEL
Manufacturer: Huizhou Bliss Commodity Co., Ltd
Category: otc | Type: HUMAN OTC DRUG LABEL
Date: 20200507

ACTIVE INGREDIENTS: ALCOHOL 70 mL/100 mL
INACTIVE INGREDIENTS: WATER; CARBOMER INTERPOLYMER TYPE A (ALLYL SUCROSE CROSSLINKED); GLYCERIN; PROPYLENE GLYCOL; SODIUM HYDROXIDE

Active ingredient

Ethyl Alcohol 70%

Purpose

Antiseptic

Use

- to reduce bacteria on the skin that could cause disease
- use when soap and water are not available.

KEEP OUT OF REACH OF CHILDREN

if swallowed, get medical help or contact a Poison Control Center right away.

warnings:

Flamable, keep away from heat and flames

For external use only: hands

Do not use:

- on children less than 2 months of age
- on open skin wounds

When using this product

- keep out of eyes. In case of contac with eyes, flush thoroughly with water
- avoid contact with broken skin
- do not inhale or ingest

Stop use and ask a doctor if

- Irritation or redness develop
- condition persists for more than 72 hours

Directions

- Wet hands thoroughly with product and rub hands until dry
- for children under 6, use only under adult supervision to avoid swallowing
- not for infants

Other information:

- do not store above 105℉
- may discolor some fabrics

Inactive ingredients

Water, glycerin, propyene glycol, carbomer, sodium hydroxide, fragrance